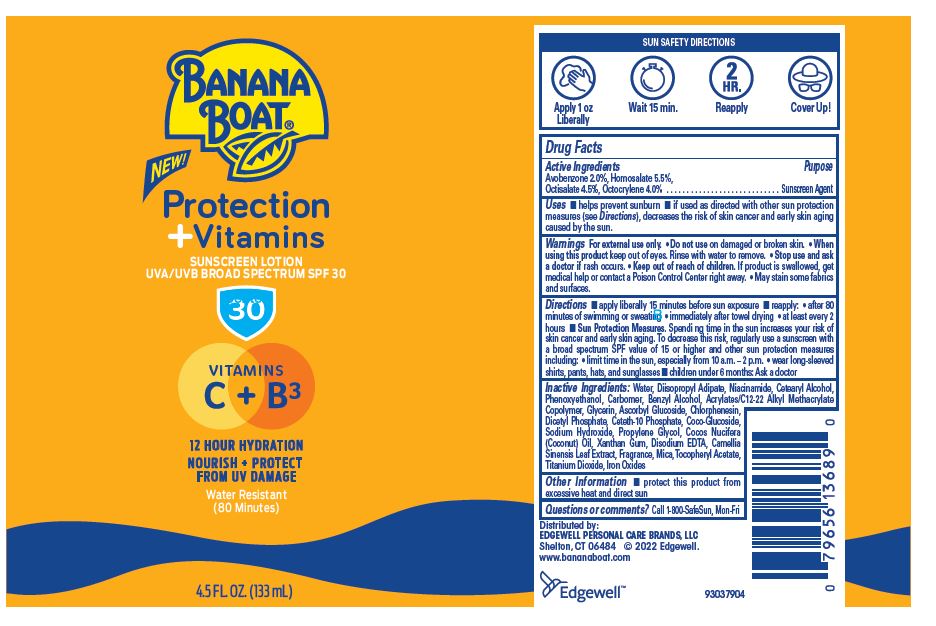 DRUG LABEL: BANANA BOAT PROTECTION PLUS VITAMINS SUNSCREEN UVA/UVB BORAD SPECTRUM SPF 30
NDC: 63354-159 | Form: LOTION
Manufacturer: Edgewell Personal Care Brands LLC
Category: otc | Type: HUMAN OTC DRUG LABEL
Date: 20241027

ACTIVE INGREDIENTS: OCTISALATE 4.5 g/100 g; AVOBENZONE 2 g/100 g; HOMOSALATE 5.5 g/100 g; OCTOCRYLENE 4 g/100 g
INACTIVE INGREDIENTS: DIISOPROPYL ADIPATE; NIACINAMIDE; ASCORBYL GLUCOSIDE; GLYCERIN; WATER; BENZYL ALCOHOL; DIHEXADECYL PHOSPHATE; COCO GLUCOSIDE; SODIUM HYDROXIDE; PROPYLENE GLYCOL; COCONUT OIL; XANTHAN GUM; EDETATE DISODIUM ANHYDROUS; CHLORPHENESIN; MICA; .ALPHA.-TOCOPHEROL ACETATE; PHENOXYETHANOL; CETETH-10 PHOSPHATE; GREEN TEA LEAF; TITANIUM DIOXIDE; CETOSTEARYL ALCOHOL

Active Ingredients

Avobenzone 2.0%, Homosalate 5.5%, Octisalate 4.5%, Octocrylene 4.0%

Purpose

Sunscreen Agent

Uses

• helps prevent sunburn • if used as directed with other sun protection measures (see Directions), decreases the risk of skin cancer and early skin aging caused by the sun.

Warnings

For external use only

• May stain some fabrics and surfaces.

Do not use

on damaged or broken skin

When using this product

keep out of eyes. Rinse with water to remove

Stop use and ask a doctor

if rash occurs.

Keep out of reach of children

If product is swallowed, get medical help or contact a Poison Control Center right away.

Directions

• apply liberally 15 minutes before sun exposure • reapply: • after 80 minutes of swimming or sweating • immediately after towel drying • at least every 2 hours • Sun Protection Measures. Spendi ng time in the sun increases your risk of skin cancer and early skin aging. To decrease this risk, regularly use a sunscreen with a broad spectrum SPF value of 15 or higher and other sun protection measures including: • limit time in the sun, especially from 10 a.m. – 2 p.m. • wear long-sleeved shirts, pants, hats, and sunglasses • children under 6 months: Ask a doctor

Inactive Ingredients

Water, Diisopropyl Adipate, Niacinamide, Cetearyl Alcohol, Phenoxyethanol, Carbomer, Benzyl Alcohol, Acrylates/C12-22 Alkyl Methacrylate Copolymer, Glycerin, Ascorbyl Glucoside, Chlorphenesin, Dicetyl Phosphate, Ceteth10 Phosphate, Coco Glucoside,
Sodium Hydroxide, Propylene Glycol, Cocos Nucifera (Coconut) Oil, Xanthan Gum, Disodium EDTA, Camellia Sinensis Leaf Extract, Fragrance, Mica, Tocopheryl Acetate, Titanium Dioxide, Iron Oxides

Other Information

protect this product from excessive heat and direct sun

Questions or comments?

Call 1-800-SafeSun, Mon-Fri

PACKAGE LABEL

BANANA

BOAT

NEW!

Protection

+ Vitamins

SUNSCREEN LOTION

UVA/UVB BROAD SPECTRUM SPF 30

30

VITAMINS

C + B 3

12 HOUR HYDRATION

NOURISH + PROTECT

FROM UV DAMAGE

Water Resistant

(80 Minutes)

4.5 FL OZ. (!33mL)